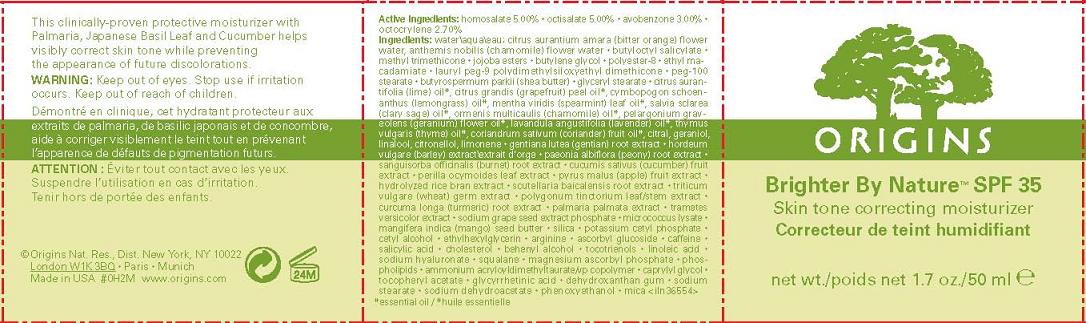 DRUG LABEL: BRIGHTER BY NATURE
NDC: 59427-703 | Form: LOTION
Manufacturer: ORIGINS NATURAL RESOURCES INC
Category: otc | Type: HUMAN OTC DRUG LABEL
Date: 20101115

ACTIVE INGREDIENTS: HOMOSALATE 5.0 mL/100 mL; OCTISALATE 5.0 mL/100 mL; AVOBENZONE 3.0 mL/100 mL; OCTOCRYLENE 2.7 mL/100 mL
INACTIVE INGREDIENTS: WATER; METHYL TRIMETHICONE; BUTYLENE GLYCOL

ACTIVE INGREDIENT

active ingredients: homosalate 5.00% [] octisalate 5.00% [] avobenzone 3.00% [] octocrylene 2.70%

INACTIVE INGREDIENT

inactive ingredients: water\aqua\eau; citrus aurantium amara (bitter orange) flower water, anthemis nobilis (chamomile) flower water [] butyloctyl salicylate [] methyl trimethicone [] jojoba esters [] butylene glycol [] polyester-8 [] ethyl macadamiate [] lauryl peg-9 polydimethylsiloxyethyl dimethicone [] peg-100 stearate [] butyrospermum parkii (shea butter) [] glyceryl stearate [] citrus aurantifolia (lime) oil*, citrus grandis (grapefruit) peel oil*, cymbopogon schoenanthus (lemongrass) oil*, mentha viridis (spearmint) leaf oil*, salvia sclarea (clary sage) oil*, ormenis multicaulis (chamomile) oil*, pelargonium graveolens (geranium) flower oil*, lavandula angustifolia (lavender) oil*, thymus vulgaris (thyme) oil*, coriandrum sativum (coriander) fruit oil*, citral, geraniol, linalool, citronellol, limonene [] gentiana lutea (gentian) root extract [] hordeum vulgare (barley) extract\extrait d'orge [] paeonia albiflora (peony) root extract [] sanguisorba officinalis (burnet) root extract [] cucumis sativus (cucumber) fruit extract [] perilla ocymoides leaf extract [] pyrus malus (apple) fruit extract [] hydrolyzed rice bran extract [] scutellaria baicalensis root extract [] triticum vulgare (wheat) germ extract [] polygonum tinctorium leaf/stem extract [] curcuma longa (turmeric) root extract [] palmaria palmata extract [] trametes versicolor extract [] sodium grape seed extract phosphate [] micrococcus lysate [] mangifera indica (mango) seed butter [] silica [] potassium cetyl phosphate [] cetyl alcohol [] ethylhexylglycerin [] arginine [] ascorbyl glucoside [] caffeine [] salicylic acid [] cholesterol [] behenyl alcohol [] tocotrienols [] linoleic acid [] sodium hyaluronate [] squalane [] magnesium ascorbyl phosphate [] phospholipids [] ammonium acryloyldimethyltaurate/vp copolymer [] caprylyl glycol [] tocopheryl acetate [] glycyrrhetinic acid [] dehydroxanthan gum [] sodium stearate [] sodium dehydroacetate [] phenoxyethanol [] mica

WARNINGS

warning: keep out of eyes. stop use if irritation occurs.

keep out of reach of children

PACKAGE LABEL

ORIGINS

BRIGHTER BY NATURE SPF 35

SKIN TONE CORRECTING MOISTURIZER

NET WT. 1.7 OZ/50 ML
ORIGINS NATURAL RES., DIST
NEW YORK, NY 10022